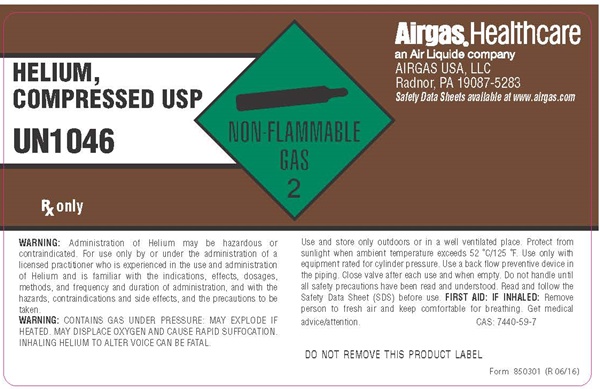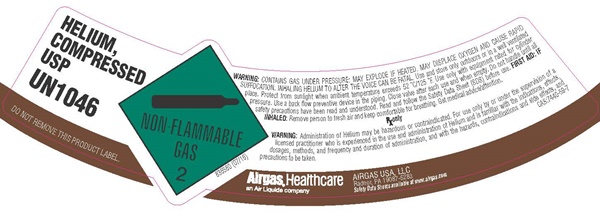 DRUG LABEL: HELIUM
NDC: 11054-004 | Form: GAS
Manufacturer: AIRGAS USA, LLC
Category: prescription | Type: HUMAN PRESCRIPTION DRUG LABEL
Date: 20250903

ACTIVE INGREDIENTS: HELIUM 992 mL/1 L

Helium, Compressed USP -004

HELIUM COMPRESSED USP SL

HELIUM,

COMPRESSED

USP

UN1046

DO NOT REMOVE THIS PRODUCT LABEL

NON-FLAMMABLE GAS 2

836580 (07/16)

WARNING: CONTAINS GAS UNDER PRESSURE. MAY EXPLODE IF HEATED. MAY DISPLACE OXYGEN AND CAUSE RAPID SUFFOCATION. INHALING HELIUM TO ALTER THE VOICE CAN BE FATAL. Use and store only outdoors or in a well ventilated place. Protect from sunlight when the ambient temperature exceeds 52°C/125°F. Use only with equipment rated for cylinder pressure. Use a back flow preventive device in the piping. Close valve after each use and when empty. Do not handle until all safety precautions have been read and understood. Read and follow the Safety Data Sheet (SDS) before use. FIRST AID: IF INHALED: Remove person to fresh air and keep comfortabe for breathing. Get medical advice/attention.

Rx only

WARNING: Administration of Helium may be hazardous or contraindicated. For use only by or under the supervision of a licensed practitioner who is experienced in the use and administration of Helium and is familiar with the indications, effects, dosages, methods, and frequency and duration of administration, and with the hazards, contraindications, and side effects and the precautions to be taken.

CAS: 7440-59-7

AIRGAS HEALTHCARE

an Air Liquide Company

AIRGAS USA, LLC
Radnor, PA 19087-5283

Safety Data Sheets available at www.airgas.com

HELIUM COMPRESSED USP body label

HELIUM,

COMPRESSED

USP

UN1046

NON-FLAMMABLE GAS 2

Rx only

WARNING: Administration of Helium may be hazardous or contraindicated. For use only by or under the supervision of a licensed practitioner who is experienced in the use and administration of Helium and is familiar with the indications, effects, dosages, methods, and frequency and duration of administration, and with the hazards, contraindications, and side effects and the precautions to be taken.

WARNING: CONTAINS GAS UNDER PRESSURE. MAY EXPLODE IF HEATED. MAY DISPLACE OXYGEN AND CAUSE RAPID SUFFOCATION. INHALING HELIUM TO ALTER THE VOICE CAN BE FATAL.

Use and store only outdoors or in a well ventilated place. Protect from sunlight when the ambient temperature exceeds 52°C/125°F. Use only with equipment rated for cylinder pressure. Use a back flow preventive device in the piping. Close valve after each use and when empty. Do not handle until all safety precautions have been read and understood. Read and follow the Safety Data Sheet (SDS) before use. FIRST AID: IF INHALED: Remove person to fresh air and keep comfortabe for breathing. Get medical advice/attention.

CAS: 7440-59-7

DO NOT REMOVE THIS PRODUCT LABEL

AIRGAS HEALTHCARE

an Air Liquide Company

AIRGAS USA, LLC
Radnor, PA 19087-5283

Safety Data Sheets available at www.airgas.com

Form 850301 (R 06/16)